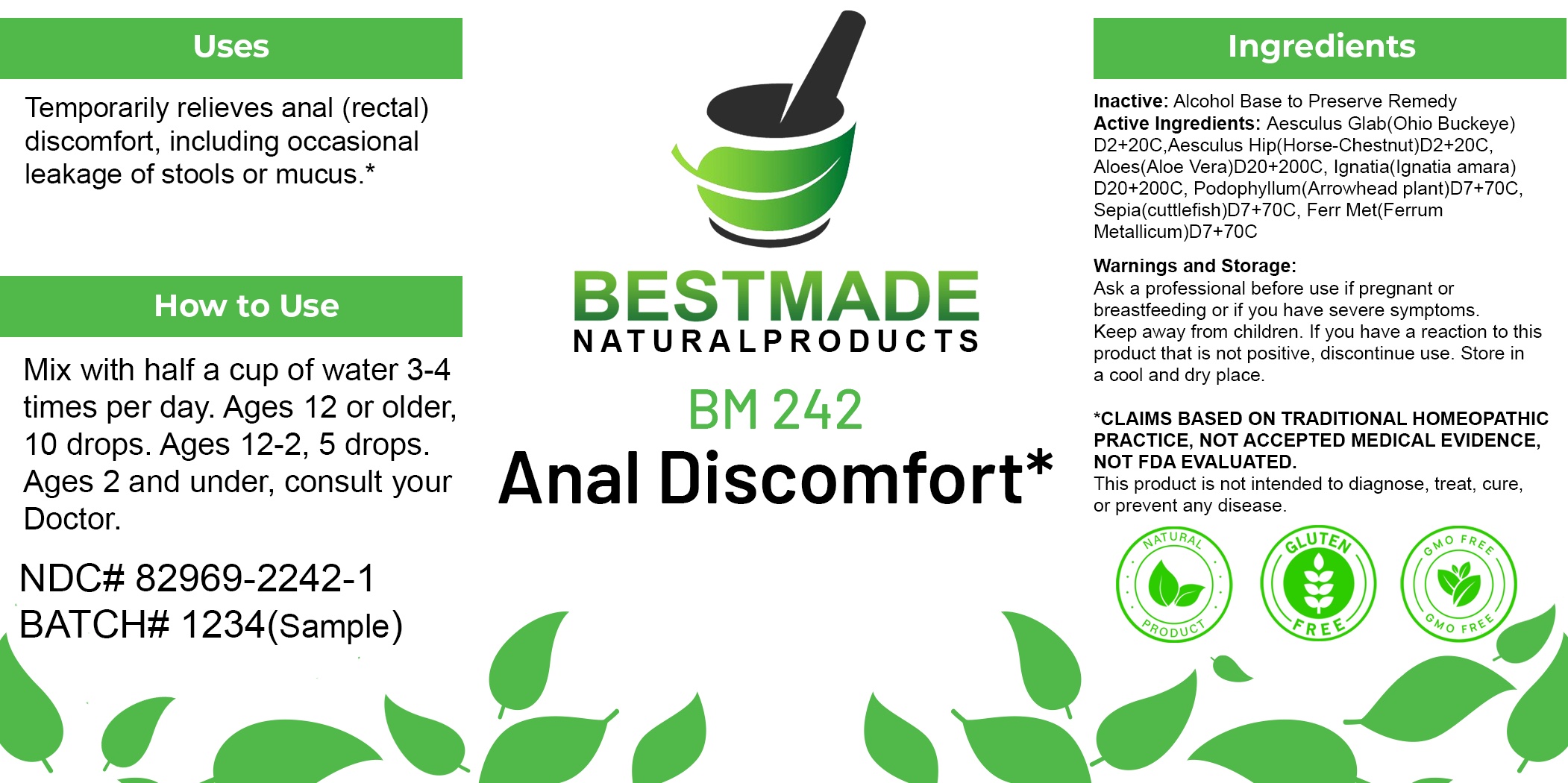 DRUG LABEL: Bestmade Natural Products BM242
NDC: 82969-2242 | Form: LIQUID
Manufacturer: Bestmade Natural Products
Category: homeopathic | Type: HUMAN OTC DRUG LABEL
Date: 20250304

ACTIVE INGREDIENTS: AESCULUS GLABRA NUT 30 [hp_C]/30 [hp_C]; ALOE VERA WHOLE 30 [hp_C]/30 [hp_C]; STRYCHNOS IGNATII SEED 30 [hp_C]/30 [hp_C]; HORSE CHESTNUT 30 [hp_C]/30 [hp_C]; SEPIA OFFICINALIS JUICE 30 [hp_C]/30 [hp_C]; IRON 30 [hp_C]/30 [hp_C]; PODOPHYLLUM 30 [hp_C]/30 [hp_C]
INACTIVE INGREDIENTS: ALCOHOL 30 [hp_C]/30 [hp_C]

BM242

DOSAGE AND ADMINISTRATION

How to Use

Mix with half a cup of water 3-4 times per day. Ages 12 or older, 10 drops. Ages 12-2, 5 drops. Ages 2 and under, consult your Doctor.

Inactive:

Alcohol Base to Preserve Product

ACTIVE INGREDIENTS
Aesculus GlabD2+20C, Aesculus HipD2+20C, AloesD20+200C, IgnatiaD20+200C, PodophyllumD7+70C, SepiaD7+70C, Ferr MetD7+70C

KEEP OUT OF REACH OF CHILDREN

Warnings and Storage:

Ask a professional before use if pregnant or breastfeeding or if you have severe symptoms.

Keep away from children. If you have a reaction to this product that is not positive, discontinue use. Store in a cool and dry place

*CLAIMS BASED ON TRADITIONAL HOMEOPATHIC PRACTICE, NOT ACCEPTED MEDICAL EVIDENCE NOT FDA EVALUATED.
This product is not intended to diagnose, treat, cure, or prevent any disease.

Warnings and Storage:

Ask a professional before use if pregnant or breastfeeding or if you have severe symptoms.

Keep away from children. If you have a reaction to this product that is not positive, discontinue use. Store in a cool and dry place

*CLAIMS BASED ON TRADITIONAL HOMEOPATHIC PRACTICE, NOT ACCEPTED MEDICAL EVIDENCE NOT FDA EVALUATED.
This product is not intended to diagnose, treat, cure, or prevent any disease.

Use:

Temporarily relieves anal (rectal) discomfort, including occasional leakage of stools or mucus.*

Use:

Temporarily relieves anal (rectal) discomfort, including occasional leakage of stools or mucus.*

Entire package label